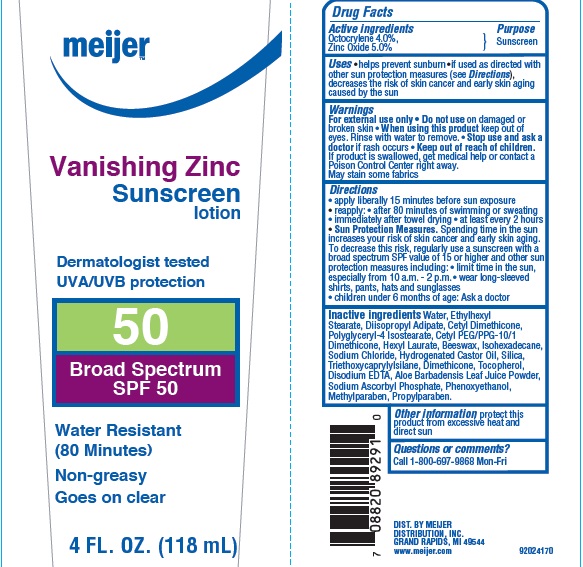 DRUG LABEL: Meijer Zinc SPF 50
                        
NDC: 41250-796 | Form: LOTION
Manufacturer: Meijer Distribution, Inc.
Category: otc | Type: HUMAN OTC DRUG LABEL
Date: 20160310

ACTIVE INGREDIENTS: OCTOCRYLENE 4 g/100 g; ZINC OXIDE  5 g/100 g
INACTIVE INGREDIENTS: WATER; ETHYLHEXYL STEARATE; DIISOPROPYL ADIPATE; POLYGLYCERYL-4 ISOSTEARATE; HEXYL LAURATE; YELLOW WAX; ISOHEXADECANE; SODIUM CHLORIDE; HYDROGENATED CASTOR OIL; SILICON DIOXIDE; TRIETHOXYCAPRYLYLSILANE; DIMETHICONE; TOCOPHEROL; EDETATE DISODIUM; ALOE VERA LEAF; SODIUM ASCORBYL PHOSPHATE; METHYLPARABEN; PROPYLPARABEN

Drug Facts

Active Ingredients

Octocrylene 4.0%, Zinc Oxide 5.0%

Purpose

Sunscreen

Uses

• helps prevent sunburn

• if used as directed with other sun protection measures (see Directions), decreases the risk of skin cancer and early skin aging caused by the sun

Warnings

For external use only

Do not use

on damaged or broken skin

When using this product

keep out of eyes. Rinse with water to remove.

Stop use and ask a doctor

if rash occurs

Keep out of reach of children.

If product is swallowed, get medical help or contact a Poison Control Center right away.

• May stain some fabrics

Directions

• apply liberally 15 minutes before sun exposure

• reapply:

• after 80 minutes of swimming or sweating

• immediately after towel drying

• at least every 2 hours

• Sun Protection Measures: Spending time in the sun increases your risk of skin cancer and early skin aging. To decrease this risk, regularly use a sunscreen with a broad spectrum SPF of 15 or higher and other sun protection measures including:

• limit time in the sun, especially from 10 a.m. to 2 p.m.

• wear long-sleeved shirts, pants, hats, and sunglasses

• children under 6 months of age: Ask a doctor

Inactive ingredients

Water, Ethylhexyl Stearate, Diisopropyl Adipate, Cetyl Dimethicone, Polyglyceryl-4 Isostearate, Cetyl PEG/PPG-10/1 Dimethicone, Hexyl Laurate, Beeswax, Isohexadecane, Sodium Chloride, Hydrogenated Castor Oil, Silica, Triethoxycaprylylsilane, Dimethicone, Tocopherol, Disodium EDTA, Aloe Barbadensis Leaf Juice Powder, Sodium Ascorbyl Phosphate, henoxyethanol, Methylparaben, Propylparaben.

Other information

protect this product from excessive heat and direct sun

Questions or comments?

Call 1-800-697-9868 Mon-Fri

Principal Display Panel

NDC: 41250-796-83

meijer

Vanishing Zinc

Sunscreen

Lotion

Dermatologist tested

UVA/UVB protection

50

Broad Spectrum

SPF 50

Water Resistant

(80 minutes)

Non-greasy

Goes on clear

4 FL. OZ. (118 mL)